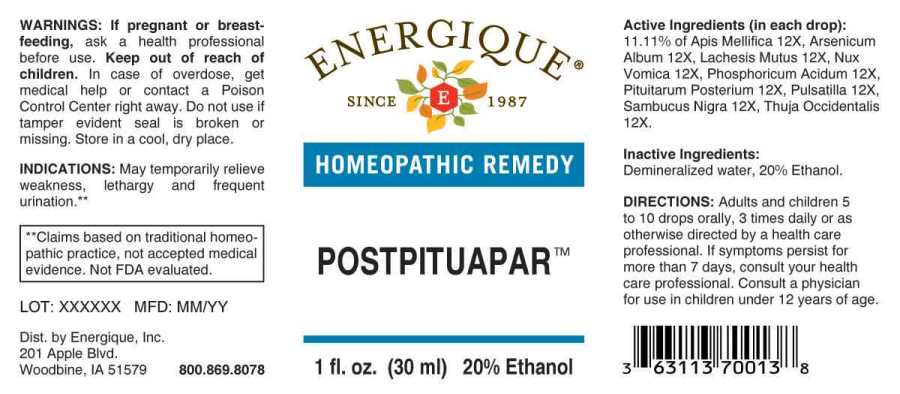 DRUG LABEL: Postpituapar
NDC: 44911-0278 | Form: LIQUID
Manufacturer: Energique, Inc.
Category: homeopathic | Type: HUMAN OTC DRUG LABEL
Date: 20241029

ACTIVE INGREDIENTS: APIS MELLIFERA 12 [hp_X]/1 mL; ARSENIC TRIOXIDE 12 [hp_X]/1 mL; LACHESIS MUTA VENOM 12 [hp_X]/1 mL; STRYCHNOS NUX-VOMICA SEED 12 [hp_X]/1 mL; PHOSPHORIC ACID 12 [hp_X]/1 mL; BOS TAURUS PITUITARY GLAND, POSTERIOR 12 [hp_X]/1 mL; PULSATILLA PRATENSIS WHOLE 12 [hp_X]/1 mL; SAMBUCUS NIGRA FLOWERING TOP 12 [hp_X]/1 mL; THUJA OCCIDENTALIS LEAFY TWIG 12 [hp_X]/1 mL
INACTIVE INGREDIENTS: WATER; ALCOHOL

DRUG FACTS:

ACTIVE INGREDIENTS:

(in each drop): 11.11% of Apis Mellifica 12X, Arsenicum Album 12X, Lachesis Mutus 12X, Nux Vomica 12X, Phosphoricum Acidum 12X, Pituitarum Posterium (Bovine) 12X, Pulsatilla (Pratensis) 12X, Sambucus Nigra 12X, Thuja Occidentalis 12X.

INDICATIONS:

May temporarily relieve weakness, lethargy and frequent urination.**

**Claims based on traditional homeopathic practice, not accepted medical evidence. Not FDA evaluated.

WARNINGS:

If pregnant or breast-feeding, ask a health professional before use.

Keep out of reach of children. In case of overdose, get medical help or contact a Poison Control Center right away.

Do not use if tamper evident seal is broken or missing. Store in a cool, dry place.

Keep out of reach of children. In case of overdose, get medical help or contact a Poison Control Center right away.

DIRECTIONS:

Adults and children 5 to 10 drops orally, 3 times daily or as otherwise directed by a health care professional. If symptoms persist for more than 7 days, consult your health care professional. Consult a physician for use in children under 12 years of age.

INDICATIONS:

May temporarily relieve weakness, lethargy and frequent urination.**

Claims based on traditional homeopathic practice, not accepted medical evidence. Not FDA evaluated.

INACTIVE INGREDIENTS:

Demineralized water, 20% Ethanol.

QUESTIONS:

Dist. by Energique, Inc.
201 Apple Blvd.
Woodbine, IA 51579 800.869.8078

PACKAGE LABEL DISPLAY:

ENERGIQUE

SINCE 1987

HOMEOPATHIC REMEDY

POSTPITUAPAR

1 fl. oz. (30 ml)